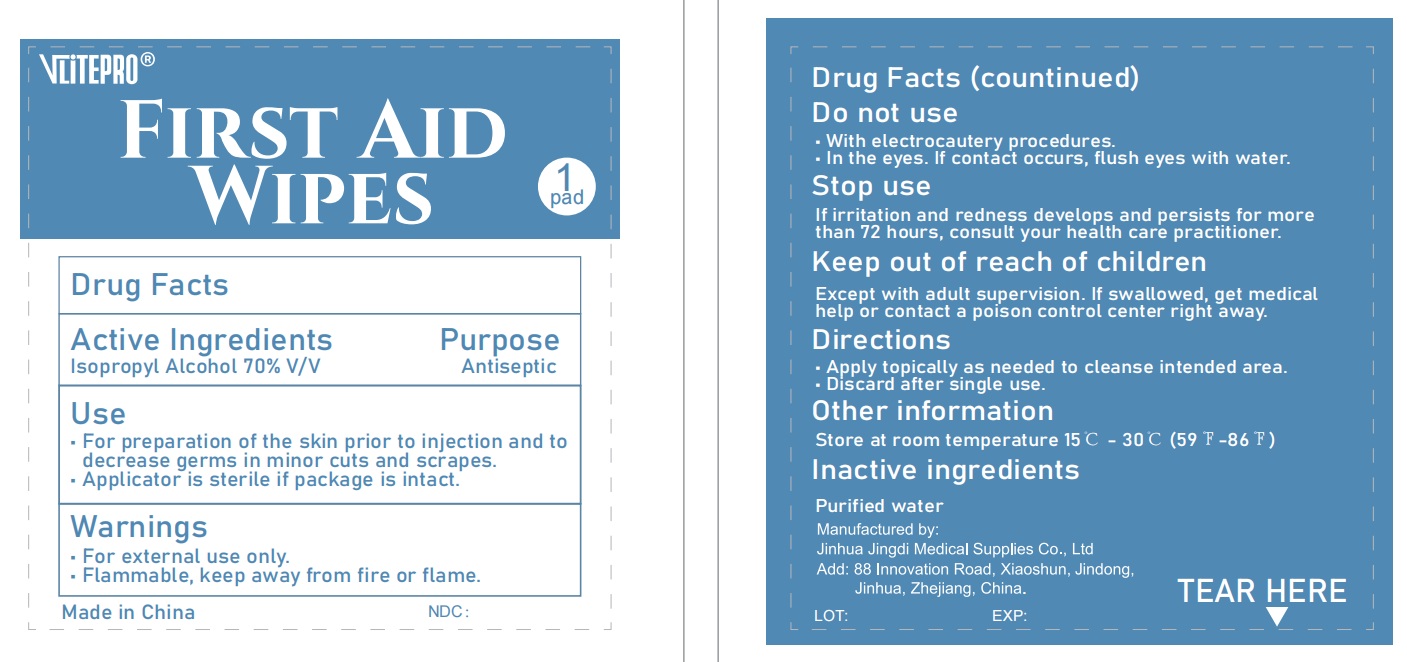 DRUG LABEL: VLITEPRO First Aid Wipes
NDC: 72459-021 | Form: CLOTH
Manufacturer: Yiwu Ori-Power Medtech Co., Ltd.
Category: otc | Type: HUMAN OTC DRUG LABEL
Date: 20250526

ACTIVE INGREDIENTS: ISOPROPYL ALCOHOL 70 mL/100 mL
INACTIVE INGREDIENTS: WATER 30 mL/100 mL

VLITEPRO First Aid Wipes

ACTIVE INGREDIENT

Isopropyl Alcohol, 70% v/v

DESCRIPTION

First aid to help prevent the risk of infection in minor cuts, scrapes, and burns.

Sterile in unopened, undamaged package.
Not made with natural rubber latex.

INACTIVE INGREDIENT

Purified Water

PURPOSE

First aid antiseptic.

First aid to help prevent the risk of infection in minor cuts, scrapes, and burns.

WARNINGS

For external use only. Flammable, keep away from fire or flame.

KEEP OUT OF REACH OF CHILDREN

If swallowed, get medical help or contact a poison control center right away.

Directions

• Apply topically as needed to cleanse intended area.

• Discard after single use.

DO NOT USE

- With electrocautery procedures.
- In the eyes. If contact occurs, flush eyes with water.

STOP USE

If irritation and redness develops and persists for more than 72 hours, consult your health care practitioner.

OTHER SAFETY INFORMATION

Store at room temperature 15 - 30°C (59 - 86°F)

DOSAGE AND ADMINISTRATION

Apply topically as needed to cleanse intendend area；
Apply the product to the skin, take the injection or puncture site as the center, slowly rotate from the insideto the outside, and gradually apply the product for two times, the disinfection area should be more than5cmx5cm, and the action time should be 1min.